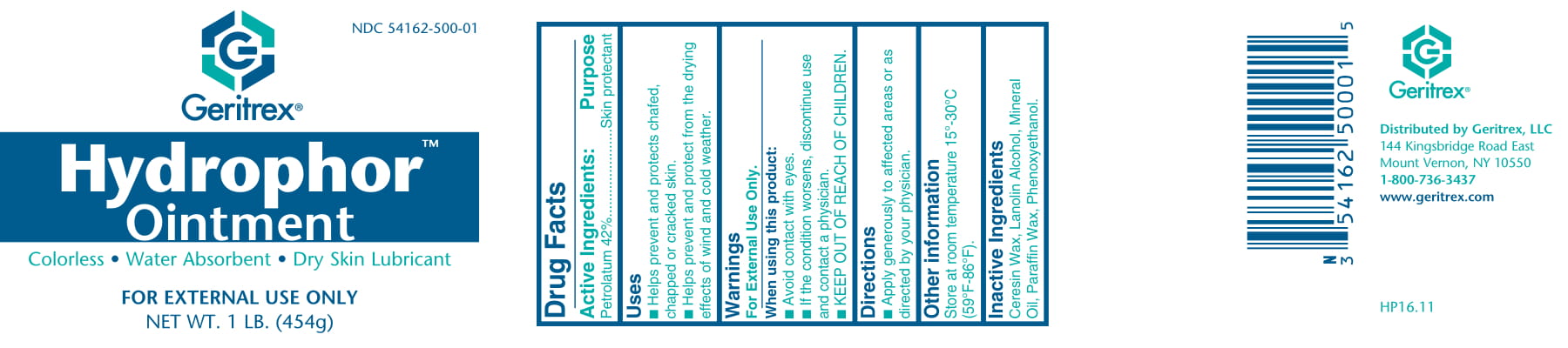 DRUG LABEL: Hydrophor
NDC: 54162-500 | Form: OINTMENT
Manufacturer: Geritrex LLC
Category: otc | Type: HUMAN OTC DRUG LABEL
Date: 20180117

ACTIVE INGREDIENTS: PETROLATUM 42 g/100 g
INACTIVE INGREDIENTS: CERESIN; LANOLIN ALCOHOLS; PARAFFIN; MINERAL OIL; PHENOXYETHANOL

Hydrophor Ointment

Drug Facts

Active Ingredients: Petrolatum 42%
Purpose: Skin protectant

Uses

• Rehydrates dry, chapped or chafed
skin.
• May be used alone as a skin lubricant
or protectant.

Directions

Apply generously to affected areas
or as directed by your physician.

DOSAGE AND ADMINISTRATION

Apply generously to affected area

Warnings

For External Use Only.
When using this product:
• Avoid contact with eyes.
• If the condition worsens,
discontinue use and contact a
physician.

Inactive Ingredient

Ceresin, Lanolin Alcohol,
Microcrystalline Wax, Mineral Oil,
Phenoxyethanol

STORAGE AND HANDLING

Store at room temperature (59°F-86°F).

KEEP OUT OF REACH OF CHILDREN.